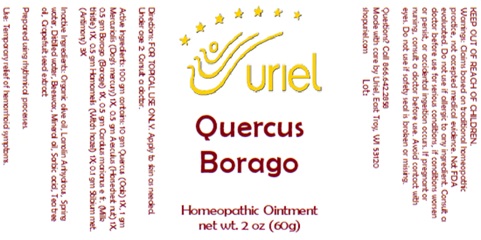 DRUG LABEL: Quercus Borago
NDC: 48951-8352 | Form: OINTMENT
Manufacturer: Uriel Pharmacy Inc.
Category: homeopathic | Type: HUMAN OTC DRUG LABEL
Date: 20250107

ACTIVE INGREDIENTS: HORSE CHESTNUT 1 [hp_X]/1 g; QUERCUS ROBUR WHOLE 1 [hp_X]/1 g; MERCURIALIS PERENNIS 1 [hp_X]/1 g; BORAGE 1 [hp_X]/1 g; MILK THISTLE 1 [hp_X]/1 g; HAMAMELIS VIRGINIANA ROOT BARK/STEM BARK 1 [hp_X]/1 g; ANTIMONY 3 [hp_X]/1 g
INACTIVE INGREDIENTS: OLIVE OIL; WATER; LANOLIN; YELLOW WAX; MINERAL OIL; CITRUS PARADISI SEED; TEA TREE OIL; SORBIC ACID

Quercus Borago

INDICATIONS AND USAGE

Directions: FOR TOPICAL USE ONLY.

DOSAGE AND ADMINISTRATION

Apply to skin as needed. Under age 2: Consult a doctor.

ACTIVE INGREDIENT

Active Ingredients: 100 gm contains: 10 gm Quercus (Oak) 1X, 1 gm Mercurialis per. (Dog’s mercury) 1X, 0.5 gm Aesculus (Horse chestnut) 1X, 0.5 gm Borago (Borage) 1X, 0.5 gm Carduus marianus (Milk thistle) 1X, 0.5 gm Hamamelis (Witch hazel) 1X; 0.1gm Stibium met. (Antimony) 3X

INACTIVE INGREDIENT

Inactive Ingredients: Organic olive oil, Lanolin Anhydrous, Spring water, Distilled water, Beeswax, Mineral oil, Sorbic acid, Tea tree oil, Grapefruit seed extract

Prepared using rhythmical processes.

PURPOSE

Use: Temporary relief of hemorrhoid symptoms.

KEEP OUT OF REACH OF CHILDREN.

WARNINGS

Warnings: Claims based on traditional homeopathic practice, not accepted medical evidence. Not FDA evaluated. Do not use if allergic to any ingredient. Consult a doctor before use for serious conditions, if conditions worsen or persist, or accidental ingestion occurs. If pregnant or nursing, consult a doctor before use. Avoid contact with eyes. Do not use if safety seal is broken or missing.

QUESTIONS

Questions? Call 866.642.2858 Made with care by Uriel, East Troy, WI 53120 shopuriel.com Lot: